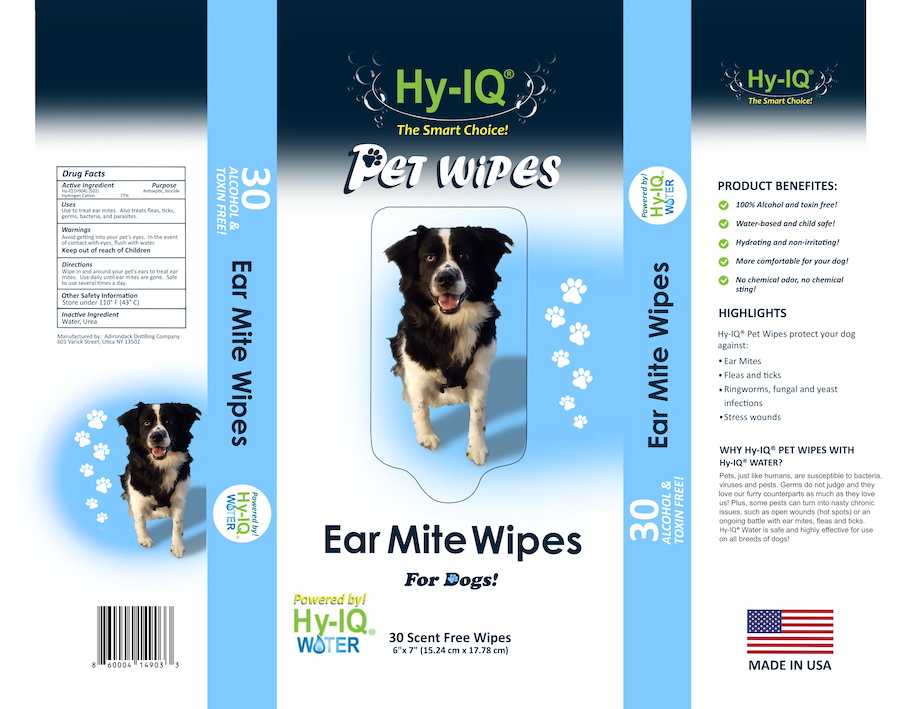 DRUG LABEL: HY IQ EAR MITE DOG WIPES
NDC: 76701-202 | Form: CLOTH
Manufacturer: HAND SANITIZER LLC
Category: animal | Type: OTC ANIMAL DRUG LABEL
Date: 20210624

ACTIVE INGREDIENTS: HYDROGEN CATION 10 mg/1 mL
INACTIVE INGREDIENTS: WATER 940 mg/1 mL; UREA 50 mg/1 mL

HY IQ EAR MITE DOG WIPES

ACTIVE INGREDIENTS

HY-IQ WATER ([H904] | [H502])

HYDROGEN CATION .77%

PURPOSE

ANTISEPTIC

USES

USE TO TREAT EAR MITES. ALSO TREATS FLEAS, TICKS, GERMS, BACTERIA AND PARASITES.

WARNINGS

AVOID GETTING INTO YOUR PET'S EYES. IN THE EVENT OF CONTACT WITH THE EYES, IMMEDIATELY FLUSH YOUR PETS'S EYES WITH WATER.
KEEP OUT OF REACH OF CHILDREN

DIRECTIONS

WIPE IN AND AROUND YOUR PET'S EARS TO TREAT EAR MITES. USE DAILY UNTIL EAR MITES ARE GONE. SAFE TO USE SEVERAL TIMES A DAY.

OTHER SAFETY INFORMATION

STORE UNDER 110 F (43 C)

INACTIVE INGREDIENT

WATER, UREA